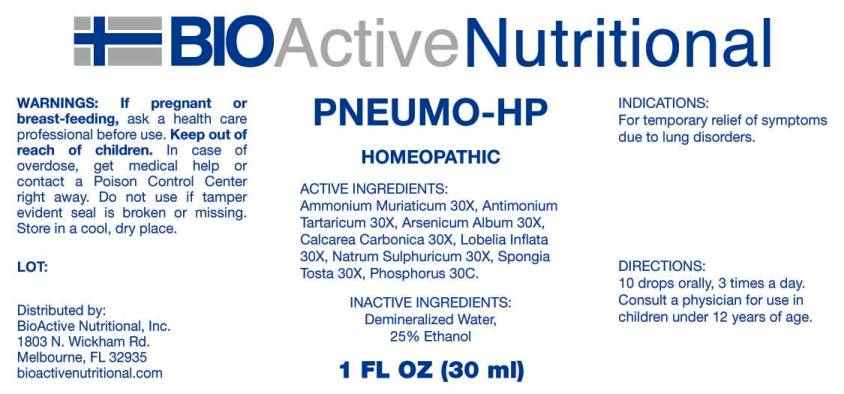 DRUG LABEL: Pneumo
NDC: 43857-0213 | Form: LIQUID
Manufacturer: BioActive Nutritional, Inc.
Category: homeopathic | Type: HUMAN OTC DRUG LABEL
Date: 20170215

ACTIVE INGREDIENTS: AMMONIUM CHLORIDE 30 [hp_X]/1 mL; ANTIMONY POTASSIUM TARTRATE 30 [hp_X]/1 mL; ARSENIC TRIOXIDE 30 [hp_X]/1 mL; OYSTER SHELL CALCIUM CARBONATE, CRUDE 30 [hp_X]/1 mL; LOBELIA INFLATA 30 [hp_X]/1 mL; SODIUM SULFATE 30 [hp_X]/1 mL; SPONGIA OFFICINALIS SKELETON, ROASTED 30 [hp_X]/1 mL; PHOSPHORUS 30 [hp_X]/1 mL
INACTIVE INGREDIENTS: WATER; ALCOHOL

DRUG FACTS:

ACTIVE INGREDIENTS:

Ammonium Muriaticum 30X, Antimonium Tartaricum 30X, Arsenicum Album 30X, Calcarea Carbonica 30X, Lobelia Inflata 30X, Natrum Sulphuricum 30X, Spongia Tosta 30X, Phosphorus 30X

INDICATIONS:

For temporary relief of symptoms due to lung disorders.

WARNINGS:

If pregnant or breast-feeding, ask a health care professional before use.

Keep out of reach of children. In case of overdose, get medical help or contact a Poison Control Center right away.

Do not use if tamper evident seal is broken or missing.

Store in a cool, dry place.

Keep out of reach of children. In case of overdose, get medical help or contact a Poison Control Center right away.

DIRECTIONS:

10 drops orally, 3 times a day. Consult a physician for use in children under 12 years of age.

INDICATIONS:

For temporary relief of symptoms due to lung disorders.

INACTIVE INGREDIENTS:

Demineralized Water, 25% Ethanol

QUESTIONS:

Distributed by:
BioActive Nutritional, Inc.
1803 N. Wickham Rd.
Melbourne, FL 32935
bioactivenutritional.com

PACKAGE LABEL DISPLAY:

BIOActive Nutritional

PNEUMO HP

HOMEOPATHIC

1 FL OZ (30 ml)